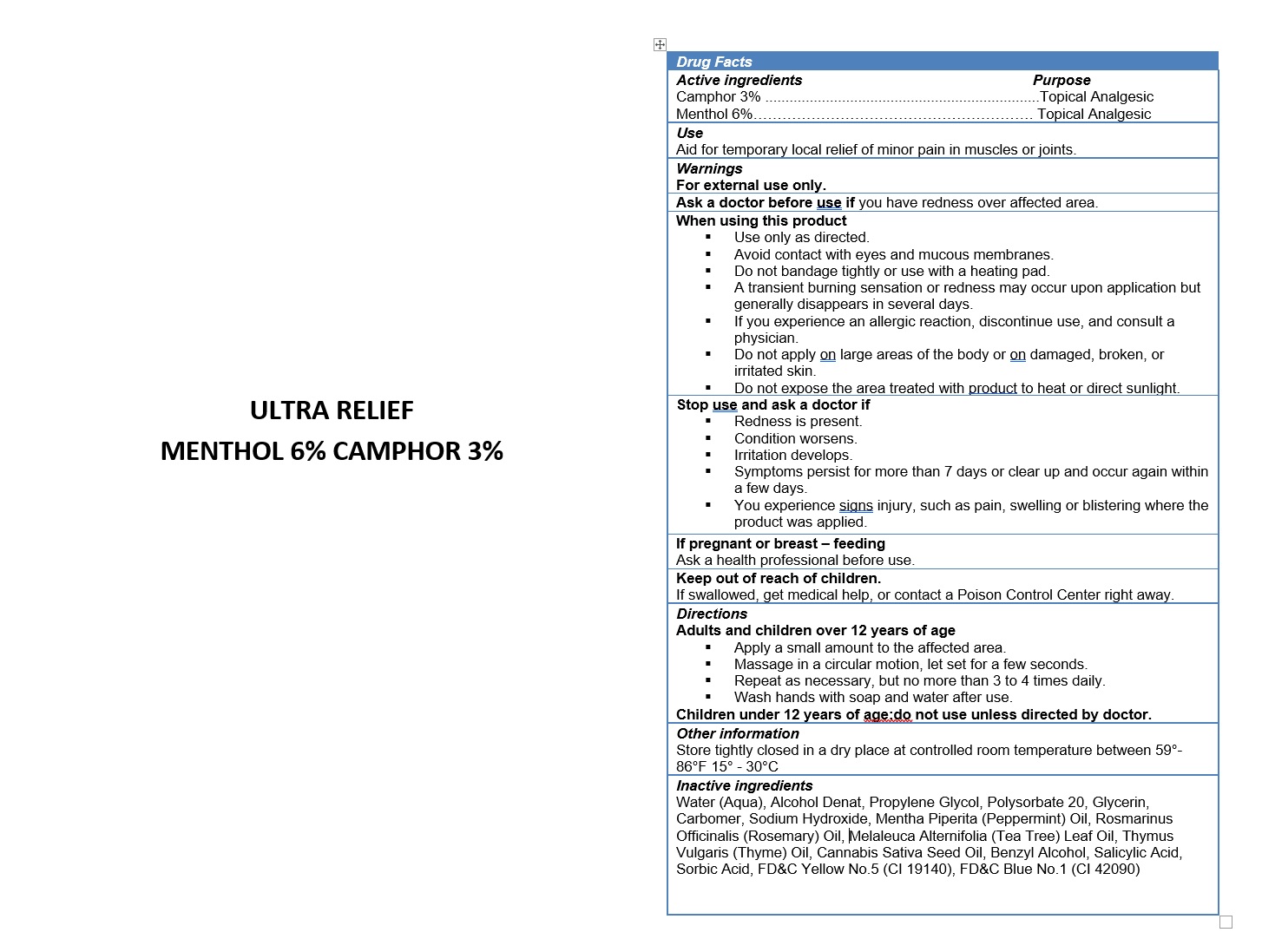 DRUG LABEL: ULTRA RELIEF
NDC: 49283-578 | Form: GEL
Manufacturer: CHEMCO CORPORATION
Category: otc | Type: HUMAN OTC DRUG LABEL
Date: 20260121

ACTIVE INGREDIENTS: MENTHOL 6 g/100 g; CAMPHOR (SYNTHETIC) 3 g/100 g
INACTIVE INGREDIENTS: CANNABIS SATIVA SEED OIL; CARBOMER 940; WATER; SODIUM HYDROXIDE; PEPPERMINT OIL; ROSEMARY OIL; THYME OIL; TEA TREE OIL; BENZYL ALCOHOL; SORBIC ACID; FD&C BLUE NO. 1; FD&C YELLOW NO. 5; ALCOHOL; PROPYLENE GLYCOL; SALICYLIC ACID; GLYCERIN; POLYSORBATE 20

49283-578-04

ACTIVE INGREDIENT

Camphor 3%

Menthol 6%

PURPOSE

Topical Analgesic.

USES:

Aid for temporary local relief of minor pain in muscles or joints.

WARNINGS

For external use only.

WHEN USING

Use only as directed.
Do not bandage tightly or use with a heating pad.
Avoid contact with eyes and mucous membranes.
Do not apply to wounds or damaged, broken, or irritated skin.
A transient burning sensation or redness may occur upon application but generally disappears in several days.
If you experience an allergic reaction, discontinue use, and consult a doctor.

Do not expose the area treated with product to heat or direct sunlight.

STOP USE AND ASK A DOCTOR IF:

Condition worsens.
Redness is present.
Irritation develops.
Symptoms persist for more than 7 days or clear up occur again within a few days.

You experience signs injury, such as pain, swelling or blistering where the product was applied.

PREGNANCY OR BREAST FEEDING

Ask a health professional before use.

KEEP OUT OF REACH OF CHILDREN

If swallowed, get medical help or contact a Poison Control Center right away.

DIRECTIONS:

Adults over 21 years:

Apply a small amount on the affected area.
Massage in circular motion, let set for a few seconds.
Repeat as neccesary, but no more than 3 to 4 times daily

Wash hands with soap and water after use.

OTHER SAFETY INFORMATION

Store tightly closed in a dry place at controlled room temperature between 59°-86° f (15°-30° c). This product is intended for use by healthy adults aged 21 years & older. consult a healthcare professional prior to use of full spectrum THC. Full spectrum THC may be harmful if you are pregnant, nursing or are taking any medication or have a medical condition.

INACTIVE INGREDIENT

Water (Aqua), Alcohol Denat, Propylene Glycol, Polysorbate 20, Glycerin, Carbomer, Sodium Hydroxide, Mentha Piperita (Peppermint) Oil, Rosmarinus Officinalis (Rosemary) Oil, Melaleuca Alternifolia (Tea Tree) Leaf Oil, Thymus Vulgaris (Thyme) Oil, Cannabis Sativa Seed Oil, Benzyl Alcohol, Salicylic Acid, Sorbic Acid, FD&C Yellow No.5 (CI 19140), FD&C Blue No.1 (CI 42090).